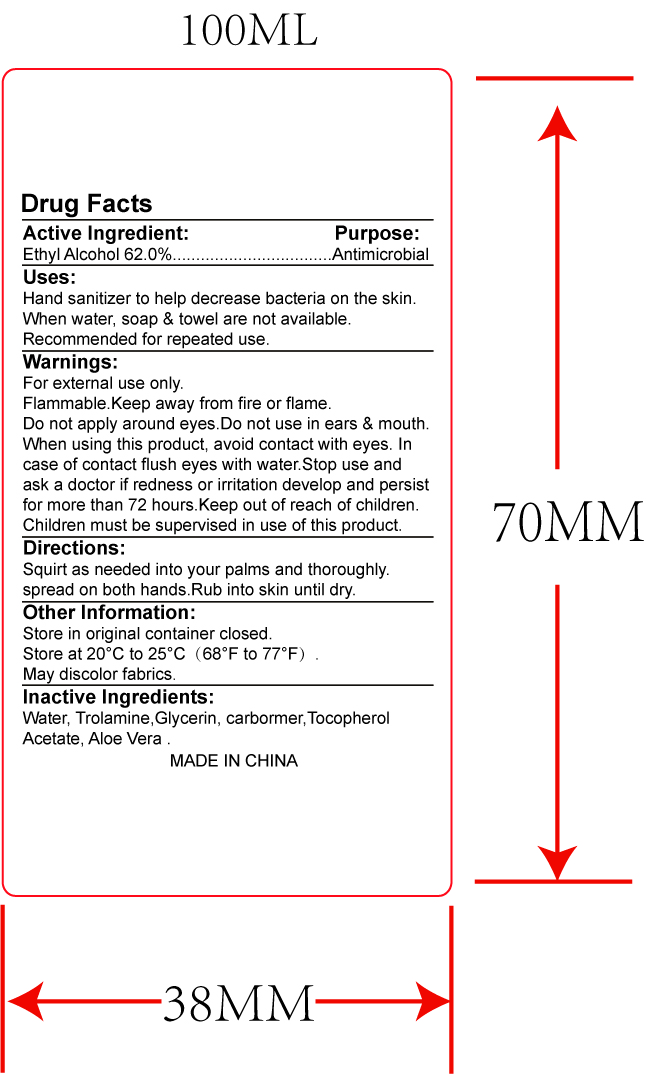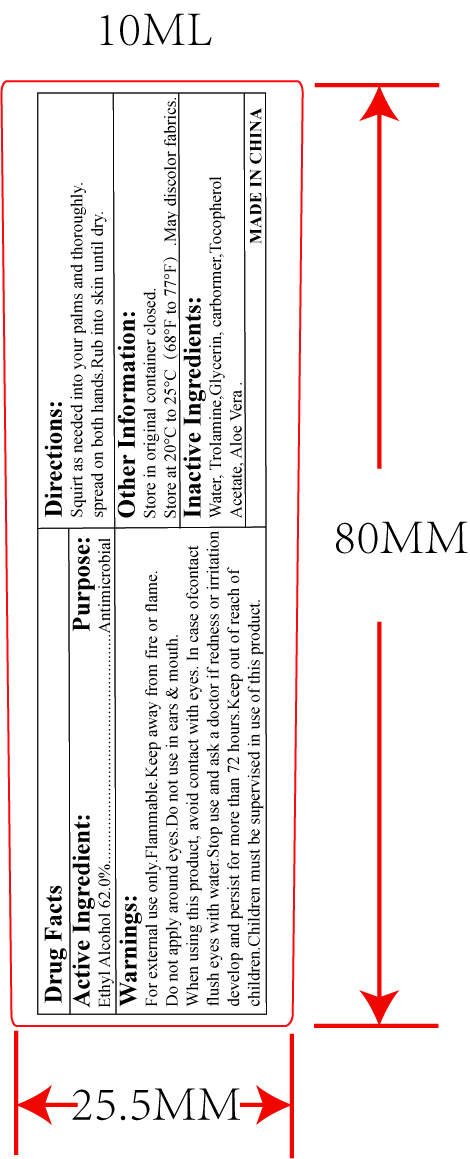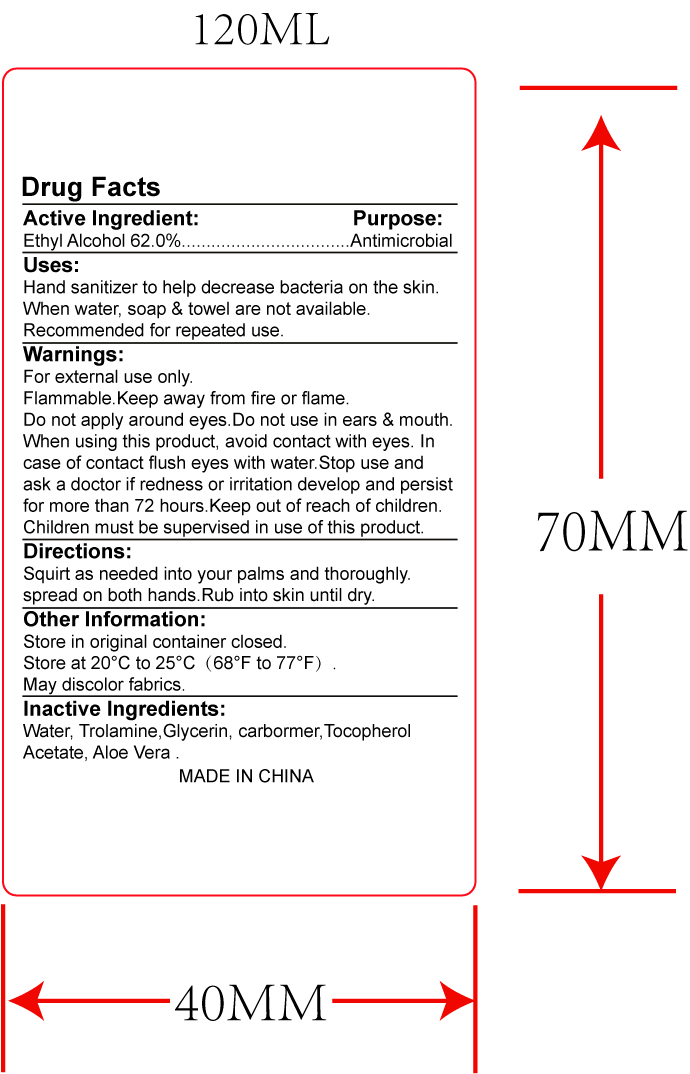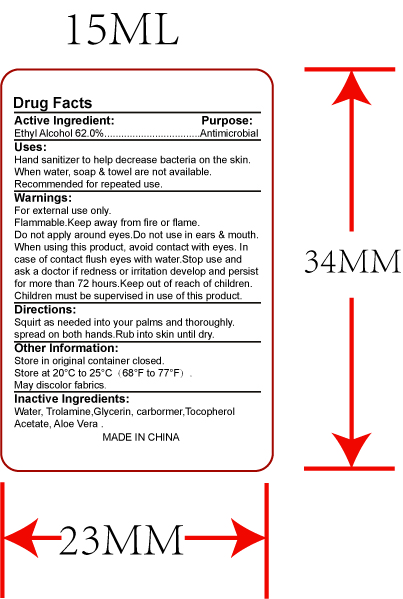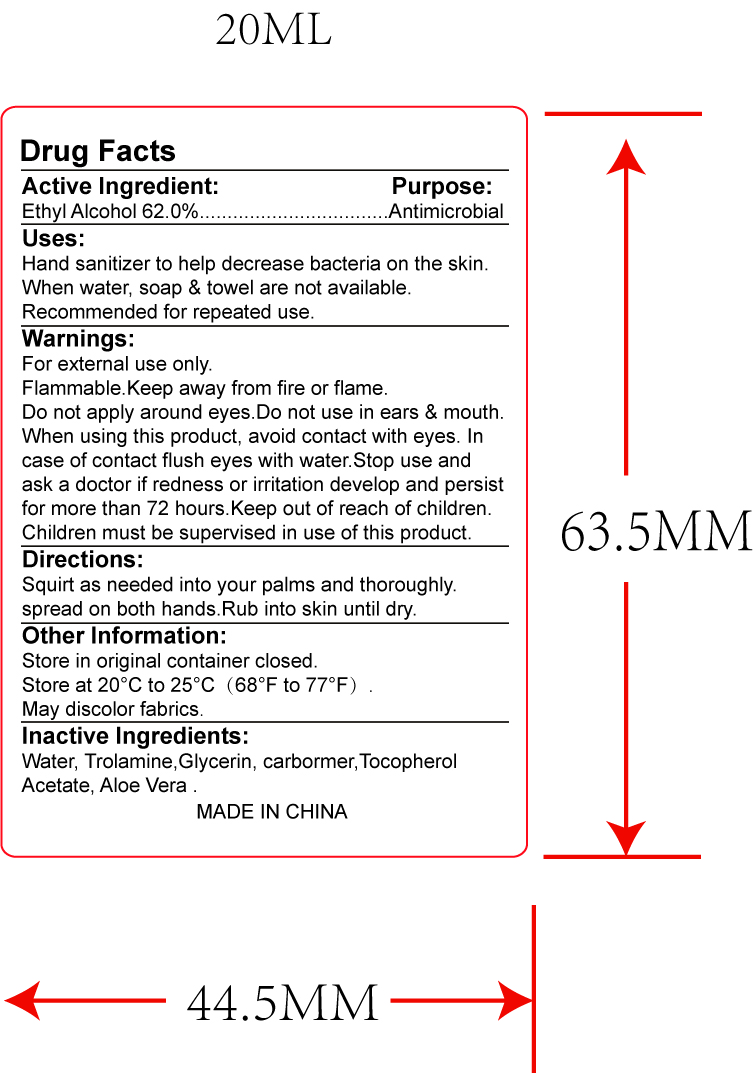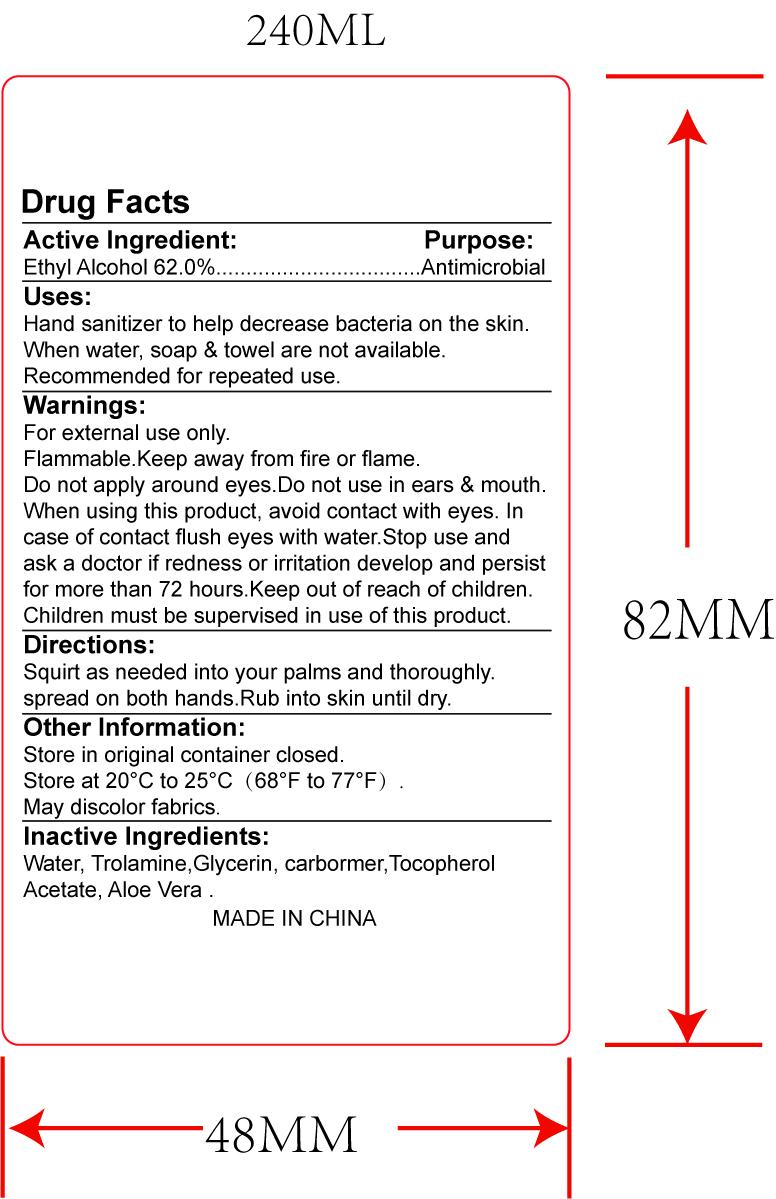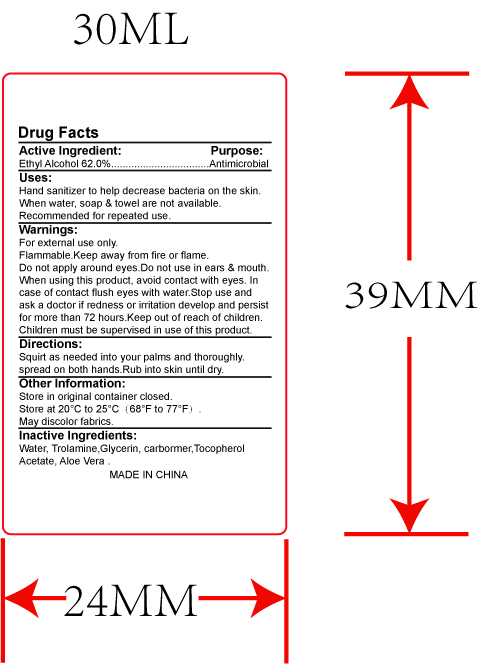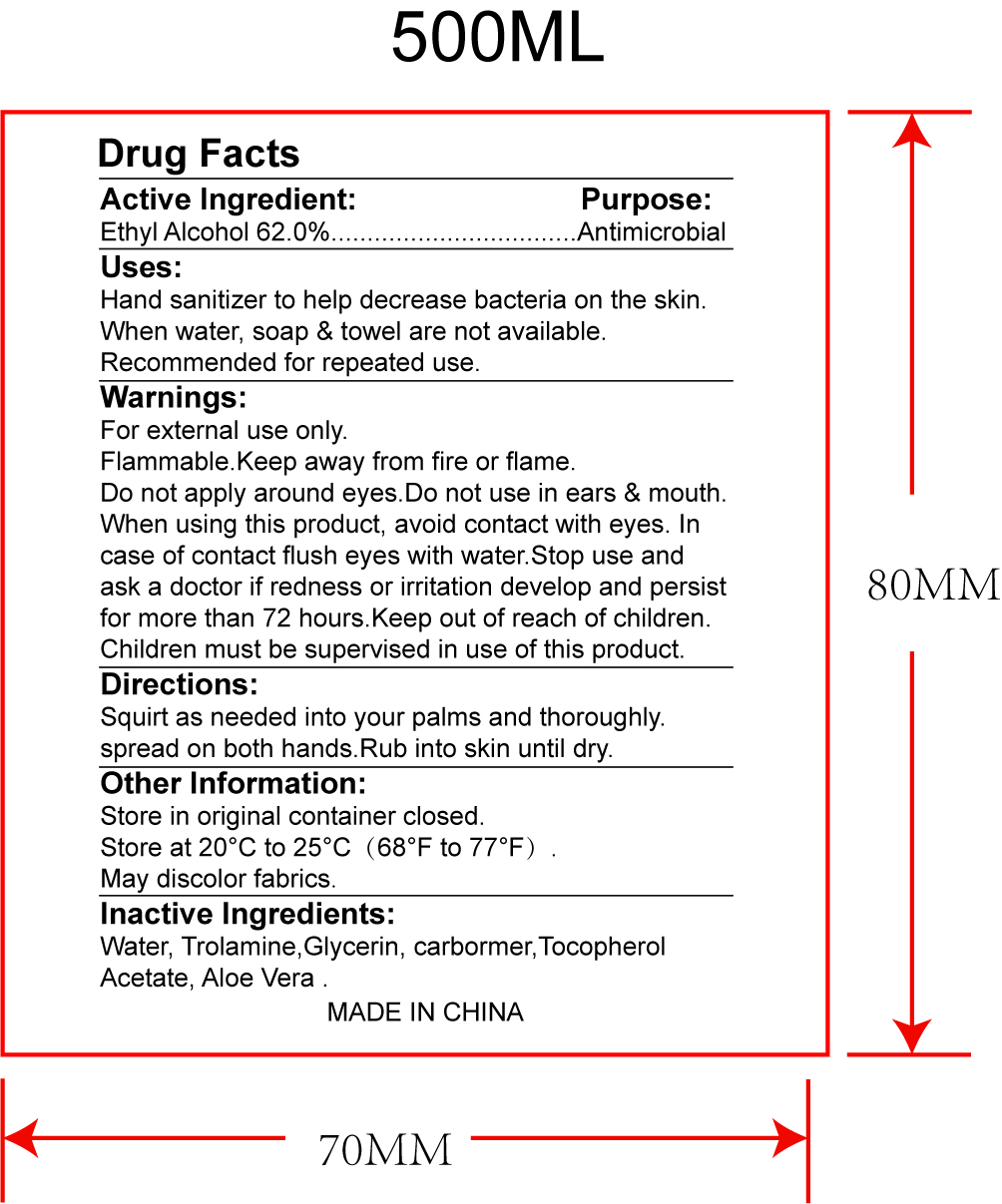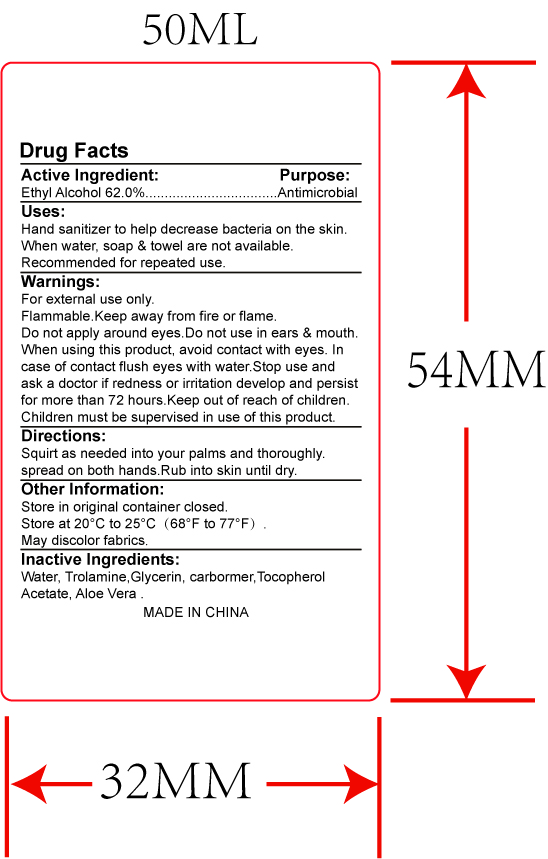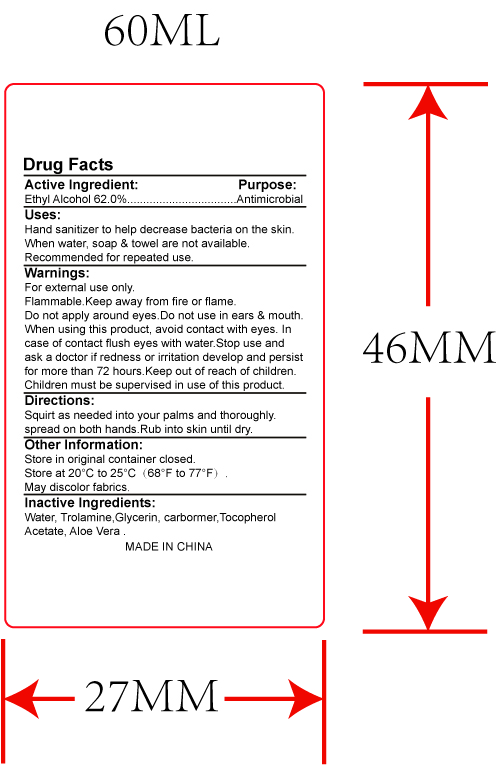 DRUG LABEL: HAND SANITIZER
NDC: 70675-001 | Form: LIQUID
Manufacturer: Deqing Jiarou Daily Chemical Co., Ltd
Category: otc | Type: HUMAN OTC DRUG LABEL
Date: 20231123

ACTIVE INGREDIENTS: ALCOHOL 62 mL/100 mL
INACTIVE INGREDIENTS: WATER; GLYCERIN; TROLAMINE; CARBOMER INTERPOLYMER TYPE A (ALLYL SUCROSE CROSSLINKED); .ALPHA.-TOCOPHEROL ACETATE, D-; ALOE VERA LEAF

Drug Facts

Active ingredient

Ethyl Alcohol 62.0%

Purpose

Antimicrobial

Keep out of reach of children.Children must be supervised in use of this product.

Uses

- Hand sanitizer to help decrease bacteria on the skin.
- When water, soap & towel are not available.
- Recommended for repeated use.

Warning

- For external use only.
- Flammable.Keep away from fire or flame.
- Do not apply around eyes.Do not use in ears & mouth.
- When using this product, avoid contact with eyes. In case of contact flush eyes with water.
- Stop use and ask a doctor if redness or irritation develop and persist for more than 72 hours.

Directions

- Squirt as needed into your palms and thoroughly spread on both hands.
- Rub into skin until dry.

OTHER SAFETY INFORMATION

- Store in original container closed.
- Store at 20°C to 25°C （68°F to 77°F）.
- May discolor fabrics.

Inactive ingredients

Water, Trolamine,Glycerin, carbormer,Tocopherol Acetate, Aloe Vera.

Packaging

NDC:70675-001-01

NDC:70675-001-02

NDC:70675-001-03

NDC:70675-001-04

NDC:70675-001-05

NDC:70675-001-06

NDC:70675-001-07

NDC:70675-001-08

NDC:70675-001-09

NDC:70675-001-10